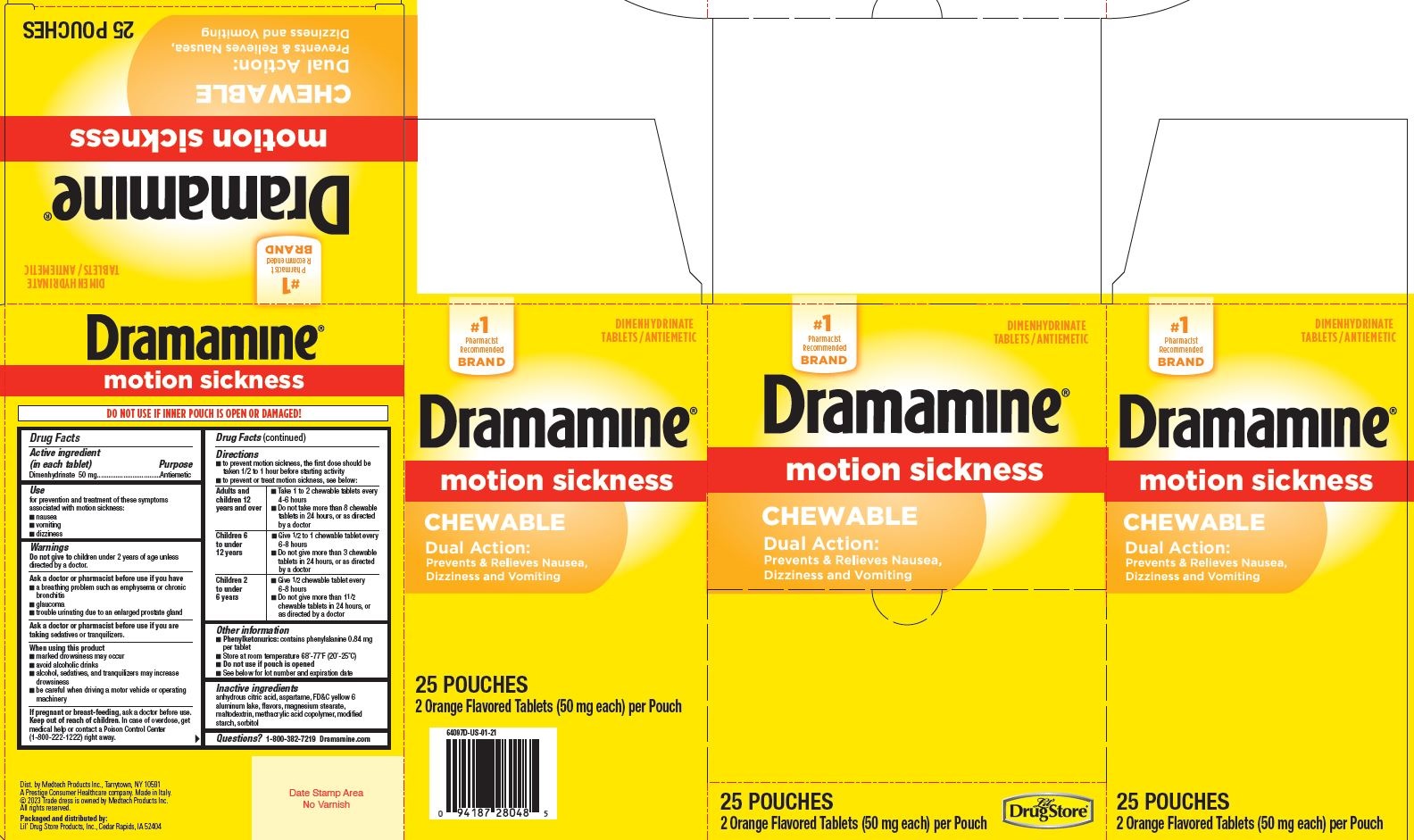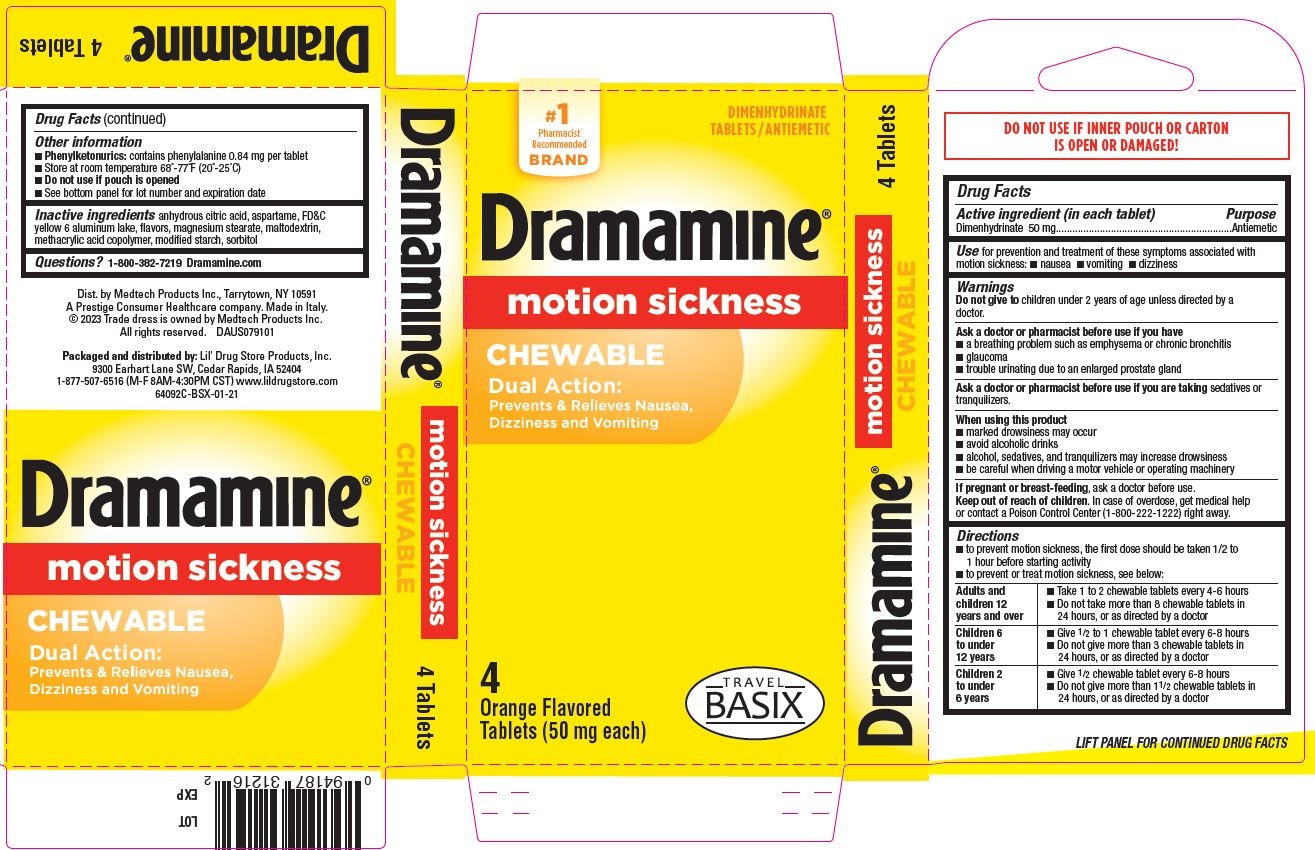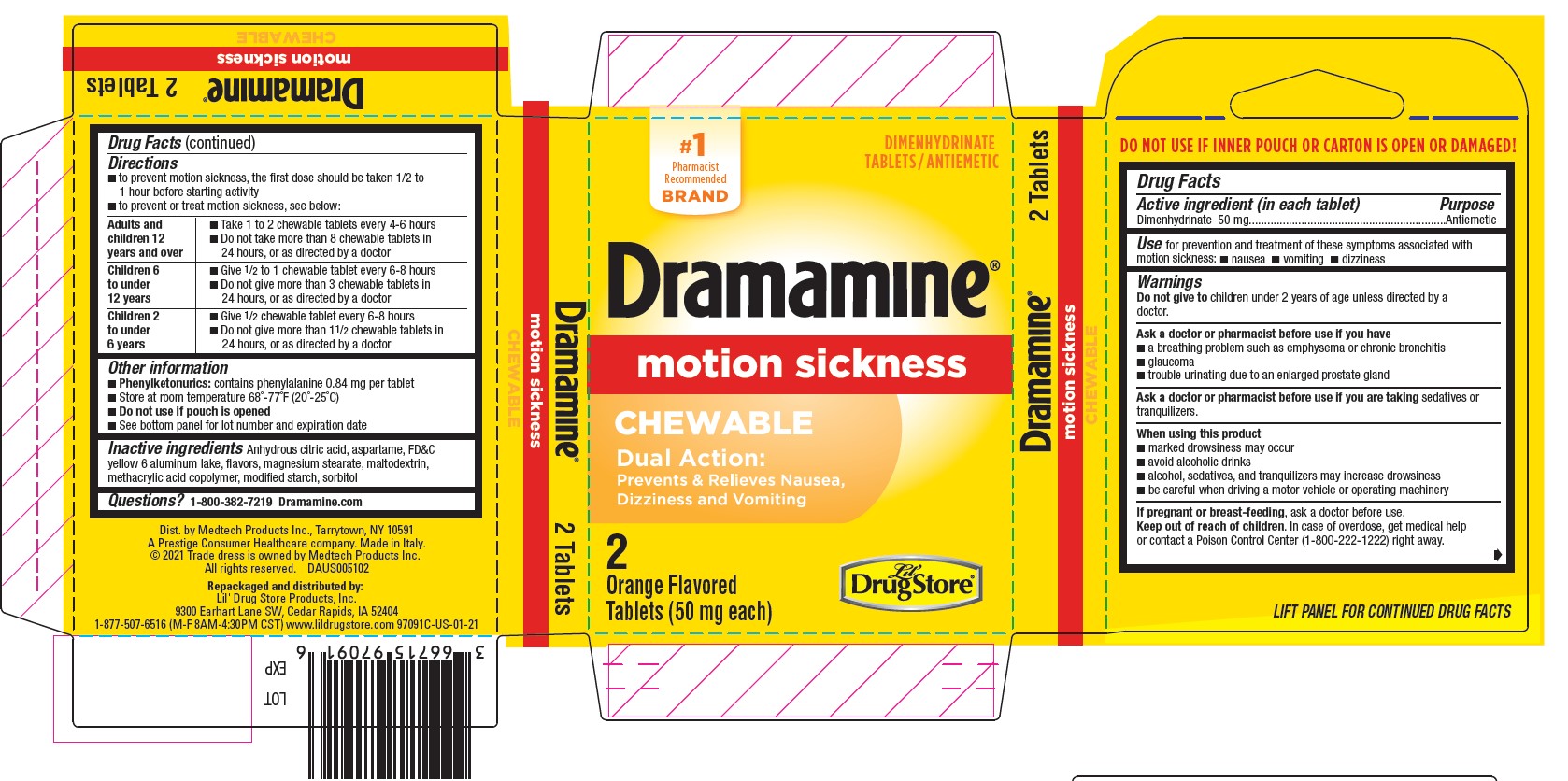 DRUG LABEL: Dramamine
NDC: 66715-9809 | Form: TABLET, CHEWABLE
Manufacturer: Lil' Drug Store Products, Inc.
Category: otc | Type: HUMAN OTC DRUG LABEL
Date: 20241126

ACTIVE INGREDIENTS: DIMENHYDRINATE 50 mg/1 1
INACTIVE INGREDIENTS: ASPARTAME; ANHYDROUS CITRIC ACID; FD&C YELLOW NO. 6; ALUMINUM OXIDE; MAGNESIUM STEARATE; MALTODEXTRIN; METHACRYLIC ACID - METHYL METHACRYLATE COPOLYMER (1:1); STARCH, CORN; SORBITOL

Dramamine® Chewable
Lil' Drug Store®, TRAVEL BASIX

Drug Facts

Active ingredient (in each tablet)

Dimenhydrinate 50 mg

Purpose

Antiemetic

Use

for prevention and treatment of these symptoms associated with motion sickness:

- nausea
- vomiting
- dizziness

Warnings

Do not use for children under 2 years of age unless directed by a doctor

Ask a doctor before use if you have

- a breathing problem such as emphysema or chronic bronchitis
- glaucoma
- trouble urinating due to an enlarged prostate gland

Ask a doctor or pharmacist before use if you are taking sedatives or tranquilizers

When using this product

- marked drowsiness may occur
- avoid alcoholic drinks
- alcohol, sedatives, and tranquilizers may increase drowsiness
- be careful when driving a motor vehicle or operating machinery

PREGNANCY OR BREAST FEEDING

If pregnant or breast-feeding, ask a doctor before use.

Keep out of reach of children. In case of accidental overdose, get medical help or contact a Poison Control Center (1-800-222-1222) right away.

Directions

- to prevent motion sickness, the first dose should be taken 1/2 to 1 hour before starting activity
- to prevent or treat motion sickness, see below:

adults and children 12 years and over | - take 1 to 2 chewable tablets every 4-6 hours - do not take more than 8 chewable tablets in 24 hours, or as directed by a doctor
children 6 to under 12 years | - give ½ to 1 chewable tablet every 6-8 hours - do not give more than 3 chewable tablets in 24 hours, or as directed by a doctor
children 2 to under 6 years | - give ½ chewable tablet every 6-8 hours - do not give more than 1-½ chewable tablets in 24 hours, or as directed by a doctor

Other information

- Phenylketonurics: contains phenylalanine 0.84 mg per tablet
- store at room temperature 68°-77°F (20°-25°C)
- do not use if packet is torn
- see bottom panel for lot number and expiration date

Inactive ingredients

anhydrous citric acid, aspartame, FD&C yellow 6 aluminum lake, flavors, magnesium stearate, maltodextrin, methacrylic acid copolymer, modified starch, sorbitol

Questions?

1-800-382-7219

Repackaged and distributed by:
Lil' Drug Store Products, Inc., 1201 Continental Place NE, Cedar Rapids, IA 52402

Dramamine® Chewable 2ct, Lil' Drug Store® - PDP/Package

#1
Pharmacist
Recommended
Brand

Dimenhydrinate
Tablets/Antiemetic

Dramamine®

motion sickness

CHEWABLE
Dual Action:

Prevents & Relieves Nausea,

Dizziness and Vomiting

2

Orange Flavored

Tablets (50 mg each)

Lil'
Drug Store®

Dramamine Chewable 4ct, TRAVEL BASIX - PDP/Package

Dramamine®

motion sickness

CHEWABLE

Dual Action:

Prevents & Relieves Nausea,Dizziness and Vomiting

4

Orange Flavored

Tablets (50 mg each)

[TRAVEL BASIX logo]

Dramamine® Chewable 25pc, Lil' Drug Store®

#1
Pharmacist
Recommended
BRAND

DIMENHYDRINATE
TABLETS /ANTIEMETIC

Dramamine ®

motion sickness

CHEWABLE
Dual Action:

Prevents & Relieves Nausea,

Dizziness and Vomiting

25 POUCHES

Orange Flavored Tablets (50 mg each) per Pouch

[Lil' Drug Store® logo]